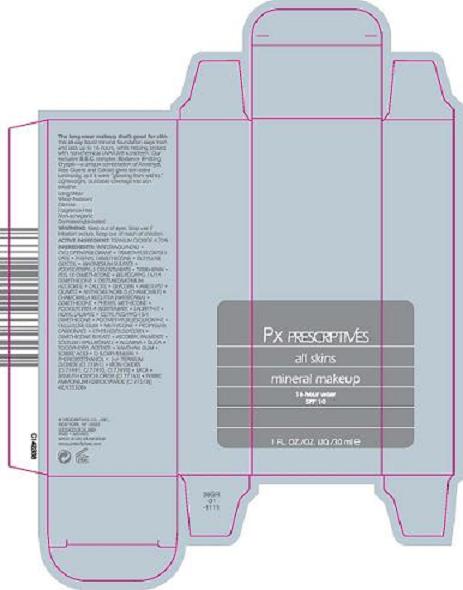 DRUG LABEL: PRESCRIPTIVES ALL SKINS MINERAL MAKEUP
NDC: 59158-723 | Form: LIQUID
Manufacturer: PRESCRIPTIVES INC
Category: otc | Type: HUMAN OTC DRUG LABEL
Date: 20100407

ACTIVE INGREDIENTS: TITANIUM DIOXIDE 4.7  mL/100 mL

ACTIVE INGREDIENT: TITANIUM DIOXIDE 4.7%

WARNINGS

WARNING: KEEP OUT OF EYES. STOP USE IF IRRITATION OCCURS.

KEEP OUT OF REACH OF CHILDREN

PACKAGE LABEL

PRINCIPAL DISPLAY PANEL
PX PRESCRIPTIVES
ALL SKINS MINERAL MAKEUP
16 HR WEAR SPF 10
1 FL OZ/OZ LIQUID/ 30 ML
PRESCRIPTIVES INC., DISTR
NEW YORK, NY 10022